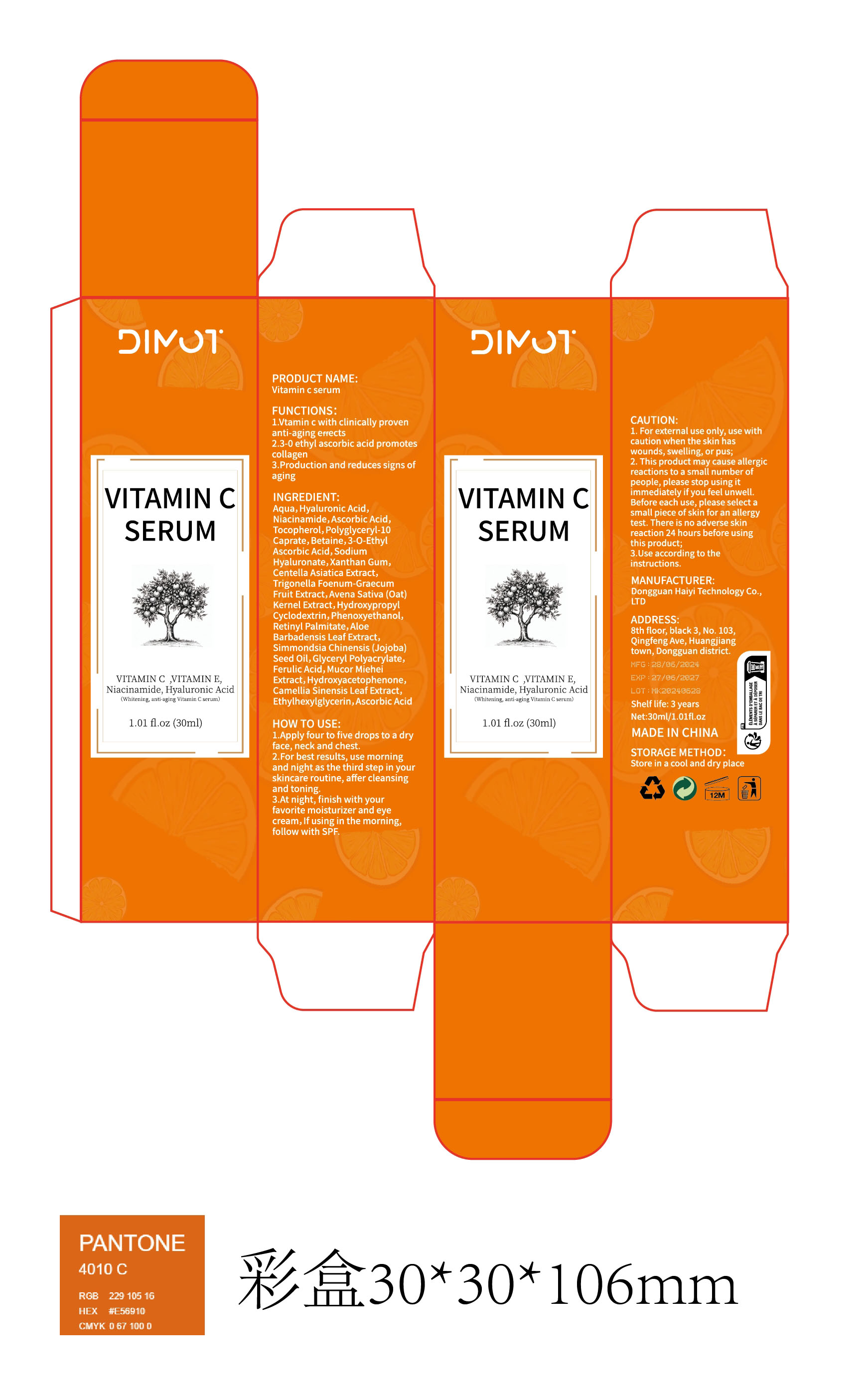 DRUG LABEL: Vitamin c serum
NDC: 84732-016 | Form: CREAM
Manufacturer: Dongguan Haiyi Technology Co.,Ltd.
Category: otc | Type: HUMAN OTC DRUG LABEL
Date: 20240926

ACTIVE INGREDIENTS: ASCORBIC ACID 1 mg/30 mL
INACTIVE INGREDIENTS: HYALURONIC ACID; BETAINE; HYALURONATE SODIUM; XANTHAN GUM; CENTELLA ASIATICA TRITERPENOIDS; HYDROXYPROPYL BETADEX; WATER; NIACINAMIDE; TOCOPHEROL; POLYGLYCERYL-10 CAPRATE; 3-O-ETHYL ASCORBIC ACID; FENUGREEK SEED; OAT

Active ingredient

Ascorbic Acid

INACTIVE INGREDIENT

Aqua, Hyaluronic Acid,Niacinamide,Tocopherol,Polyglyceryl-10Caprate,Betaine,3-0-EthylAscorbic Acid, SodiumHyaluronate,Xanthan Gum,Centella Asiatica Extract,Trigonella Foenum-GraecumFruit Extract,Avena Sativa (Oat)Kernel Extract,HydroxypropylCyclodextrin,Phenoxyethanol,Retinyl Palmitate,AloeBarbadensis Leaf Extract,Simmondsia Chinensis (Jojoba)Seed oil,Glyceryl Polyacrylate,Ferulic Acid,Mucor MieheiExtract,Hydroxyacetophenone,Camellia Sinensis Leaf Extract,Ethylhexylglycerin,Ascorbic Acid

Purpose section

1.Vtamin c with clinically provenanti-aging erects

2.3-0 ethyl ascorbic acid promotescollagen

3.Production and reduces signs ofaging

Warning

1. For external use only, use withcaution when the skin haswounds, swelling, or pus;2. This product may cause allergicreactions to a small number ofpeople, please stop using itimmediately if you feel unwell.Before each use, please select asmall piece of skin for an allergytest. There is no adverse skinreaction 24 hours before usingthis product;3.Use according to theinstructions.

stop use

This product may cause allergic reactions in asmall number of people.
lf youexperience any discomfort,please stop using it immediately.

not use

Not suitable for use by children, pregnantor breast feeding people.

OUT OF CHILDREN

KEEP THE PRODUCT OUT OF REACH OF CHILDREN to

HOW TO USE

1.Apply four to five drops to a dryface, neck and chest.

2.For best results, use morningand night as the third step in yourskincare routine, affer cleansingand toning.

3.At night, finish with yourfavorite moisturizer and eyecream,lf using in the morning,follow with SPF.

Dosage

take an appropriateamount,Use 2-3 times a week